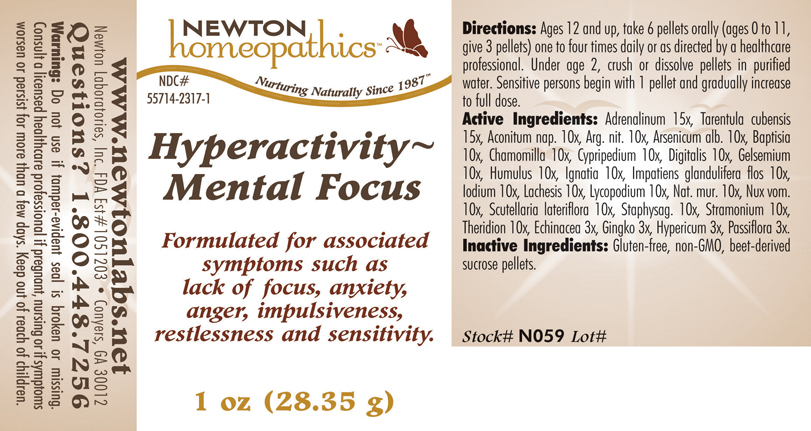 DRUG LABEL: Hyperactivity - Mental Focus 
NDC: 55714-2317 | Form: PELLET
Manufacturer: Newton Laboratories, Inc.
Category: homeopathic | Type: HUMAN OTC DRUG LABEL
Date: 20110301

ACTIVE INGREDIENTS: Epinephrine 15 [hp_X]/1 g; Citharacanthus Spinicrus 15 [hp_X]/1 g; Aconitum Napellus 10 [hp_X]/1 g; Silver Nitrate 10 [hp_X]/1 g; Arsenic Trioxide 10 [hp_X]/1 g; Baptisia Tinctoria 10 [hp_X]/1 g; Matricaria Recutita 10 [hp_X]/1 g; Cypripedium Parvifolum Root 10 [hp_X]/1 g; Digitalis 10 [hp_X]/1 g; Gelsemium Sempervirens Root 10 [hp_X]/1 g; Hops 10 [hp_X]/1 g; Strychnos Ignatii Seed 10 [hp_X]/1 g; Impatiens Glandulifera Flower 10 [hp_X]/1 g; Iodine 10 [hp_X]/1 g; Lachesis Muta Venom 10 [hp_X]/1 g; Lycopodium Clavatum Spore 10 [hp_X]/1 g; Sodium Chloride 10 [hp_X]/1 g; Strychnos Nux-vomica Seed 10 [hp_X]/1 g; Scutellaria Lateriflora 10 [hp_X]/1 g; Delphinium Staphisagria Seed 10 [hp_X]/1 g; Datura Stramonium 10 [hp_X]/1 g; Theridion Curassavicum 10 [hp_X]/1 g; Echinacea, Unspecified 3 [hp_X]/1 g; Ginkgo 3 [hp_X]/1 g; Hypericum Perforatum 3 [hp_X]/1 g; Passiflora Incarnata Flowering Top 3 [hp_X]/1 g
INACTIVE INGREDIENTS: Sucrose

Hyperactivity - Mental Focus

INDICATIONS & USAGE SECTION

Hyperactivity - Mental Focus Formulated for associated symptoms such as lack of focus, anxiety, anger, impulsiveness, restlessness and sensitivity.

DOSAGE & ADMINISTRATION SECTION

Directions: Ages 12 and up, take 6 pellets orally (ages 0 to 11, give 3 pellets) one to four times daily or as directed by a healthcare professional. Under age 2, crush or dissolve pellets in purified water. Sensitive persons begin with 1 pellet and gradually increase to full dose.

OTC - ACTIVE INGREDIENT SECTION

Adrenalinum 15x, Tarentula cubensis15x, Aconitum nap. 10x, Arg. nit. 10x, Arsenicum alb. 10x, Baptisia 10x, Chamomilla 10x, Cypripedium 10x, Digitalis 10x, Gelsemium 10x, Humulus 10x, Ignatia 10x, Impatiens glandulifera flos 10x, Iodium 10x, Lachesis 10x, Lycopodium 10x, Nat. mur. 10x, Nux vom.10x, Scutellaria lateriflora 10x, Staphysag. 10x, Stramonium 10x, Theridion 10x, Echinacea 3x, Gingko 3x, Hypericum 3x, Passiflora 3x.

OTC - PURPOSE SECTION

Formulated for associated symptoms such as lack of focus, anxiety, anger, impulsiveness, restlessness and sensitivity.

INACTIVE INGREDIENT SECTION

Inactive Ingredients: Gluten-free, non-GMO, beet-derived sucrose pellets.

QUESTIONS SECTION

www.newtonlabs.net Newton Laboratories, Inc. FDA Est # 1051203 - Conyers, GA 30012
Questions? 1.800.448.7256

WARNINGS SECTION

Warning: Do not use if tamper - evident seal is broken or missing. Consult a licensed healthcare professional if pregnant, nursing or if symptoms worsen or persist for more than a few days. Keep out of reach of children.

OTC - PREGNANCY OR BREAST FEEDING SECTION

Consult a licensed healthcare professional if pregnant, nursing or if symptoms worsen or persist for more than a few days.

OTC - KEEP OUT OF REACH OF CHILDREN SECTION

Keep out of reach of children.